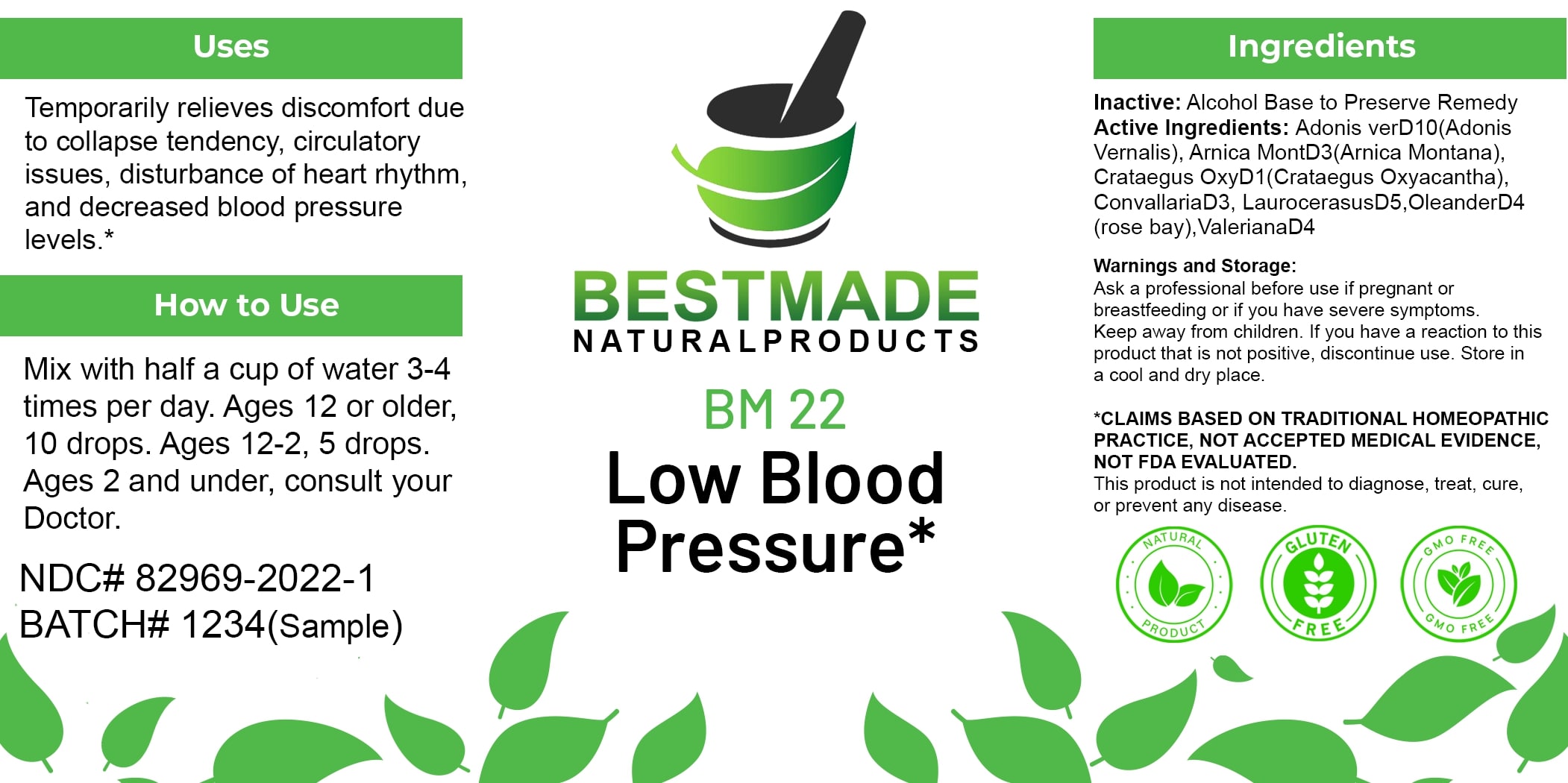 DRUG LABEL: Bestmade Natural Products BM22
NDC: 82969-2022 | Form: LIQUID
Manufacturer: Bestmade Natural Products
Category: homeopathic | Type: HUMAN OTC DRUG LABEL
Date: 20250123

ACTIVE INGREDIENTS: ADONIS VERNALIS 30 [hp_C]/30 [hp_C]; ARNICA MONTANA 30 [hp_C]/30 [hp_C]; HAWTHORN LEAF WITH FLOWER 30 [hp_C]/30 [hp_C]; CONVALLARIA MAJALIS 30 [hp_C]/30 [hp_C]; PRUNUS LAUROCERASUS LEAF 30 [hp_C]/30 [hp_C]; NERIUM OLEANDER LEAF 30 [hp_C]/30 [hp_C]; VALERIAN 30 [hp_C]/30 [hp_C]
INACTIVE INGREDIENTS: ALCOHOL 30 [hp_C]/30 [hp_C]

BM22

DOSAGE AND ADMINISTRATION

How to Use

Mix with half a cup of water 3-4 times per day. Ages 12 or older, 10 drops. Ages 12-2, 5 drops. Ages 2 and under, consult your Doctor.

INACTIVE INGREDIENT

Ingredients

Inactive: Alcohol Base to Preserve Remedy

Uses

Temporarily relieves discomfort due to collapse tendency, circulatory issues, disturbance of heart rhythm, and decreased blood pressure levels.*

*CLAIMS BASED ON TRADITIONAL HOMEOPATHIC PRACTICE, NOT ACCEPTED MEDICAL EVIDENCE. NOT FDA EVALUATED.

This product is not intended to diagnose, treat, cure, or prevent any disease.

Uses

Temporarily relieves discomfort due to collapse tendency, circulatory issues, disturbance of heart rhythm, and decreased blood pressure levels.*

*CLAIMS BASED ON TRADITIONAL HOMEOPATHIC PRACTICE, NOT ACCEPTED MEDICAL EVIDENCE. NOT FDA EVALUATED.

This product is not intended to diagnose, treat, cure, or prevent any disease.

Active Ingredients:

Adonis verD10(Adonis Vernalis), Arnica MontD3(Arnica Montana), Crataegus OxyD1(Crataegus Oxyacantha), ConvallariaD3, LaurocerasusD5, OleanderD4 (rose bay), ValerianaD4

KEEP OUT OF REACH OF CHILDREN

Warnings and Storage:

Ask a professional before use if pregnant or breastfeeding or if you have severe symptoms. Keep away from children. If you have a reaction to this product that is not positive, discontinue use. Store in a cool and dry place.

Warnings and Storage:

Ask a professional before use if pregnant or breastfeeding or if you have severe symptoms. Keep away from children. If you have a reaction to this product that is not positive, discontinue use. Store in a cool and dry place.

*CLAIMS BASED ON TRADITIONAL HOMEOPATHIC PRACTICE, NOT ACCEPTED MEDICAL EVIDENCE. NOT FDA EVALUATED.

This product is not intended to diagnose, treat, cure, or prevent any disease.

Entire package label